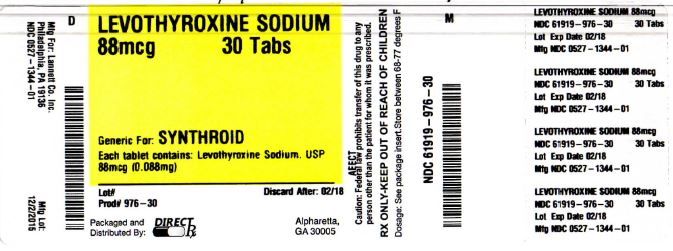 DRUG LABEL: LEVOTHYROXINE SODIUM
NDC: 61919-976 | Form: TABLET
Manufacturer: DirectRX
Category: prescription | Type: HUMAN PRESCRIPTION DRUG LABEL
Date: 20151203

ACTIVE INGREDIENTS: LEVOTHYROXINE SODIUM 0.088 mg/1 1
INACTIVE INGREDIENTS: LACTOSE; CELLULOSE, MICROCRYSTALLINE; ACACIA; MAGNESIUM STEARATE; SILICON DIOXIDE; SODIUM STARCH GLYCOLATE TYPE A POTATO; FD&C YELLOW NO. 6; FD&C BLUE NO. 1; D&C YELLOW NO. 10; ALUMINUM OXIDE; STARCH, CORN

LEVOTHYROXINE SODIUM